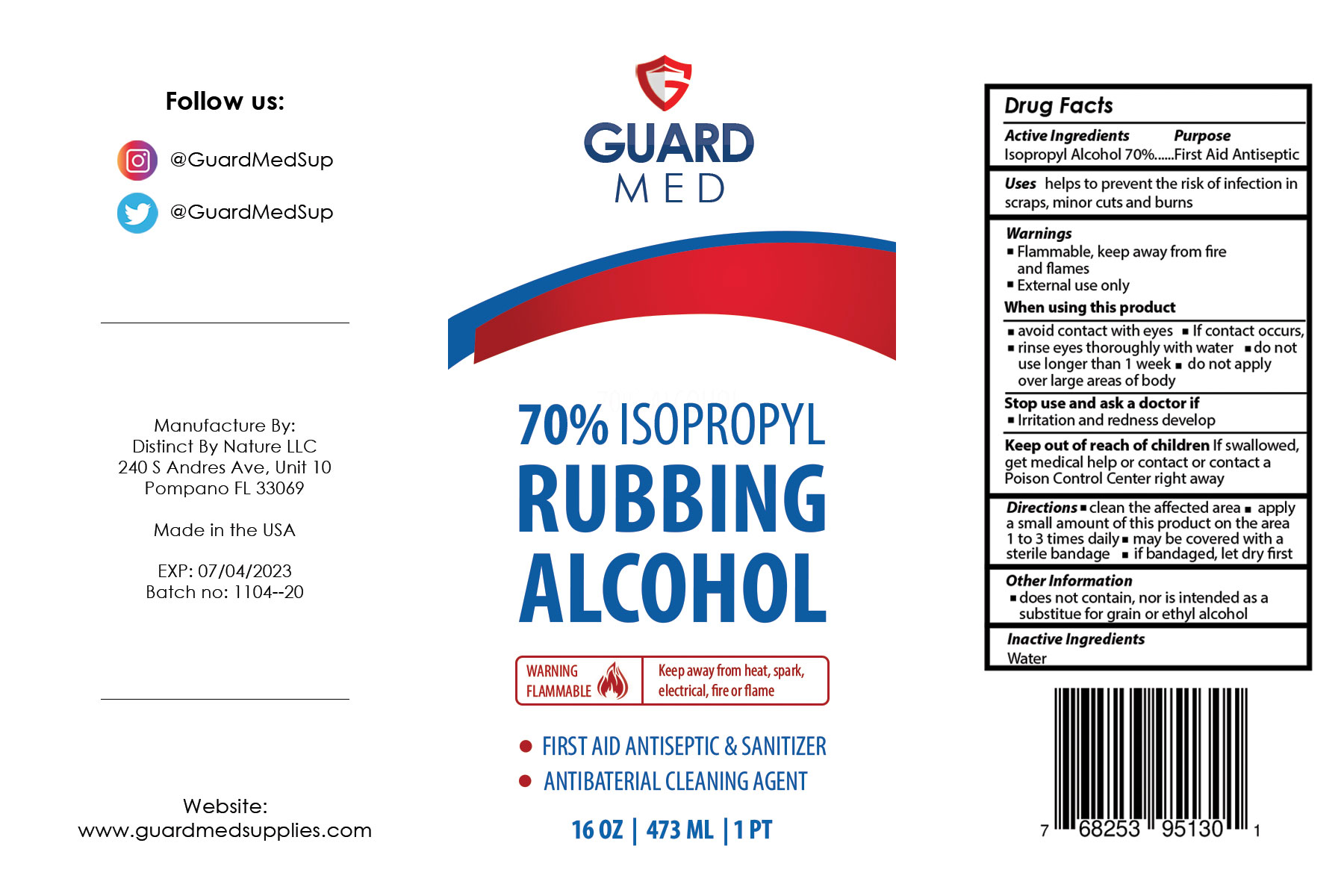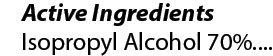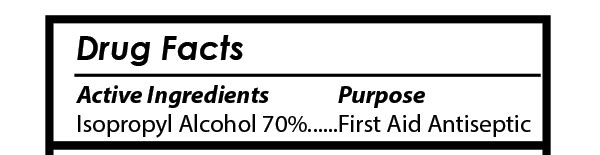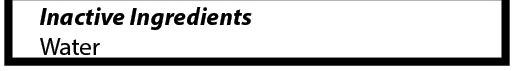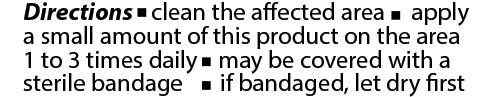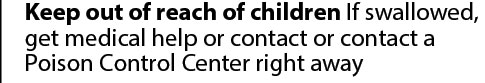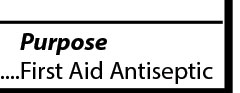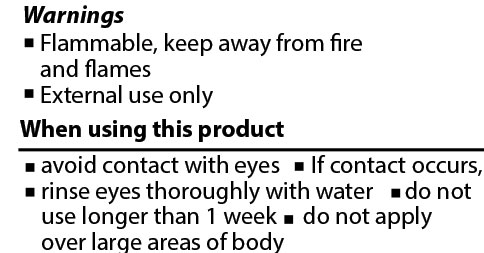 DRUG LABEL: GuardMed 70% Rubbing Alcohol
NDC: 74697-101 | Form: LIQUID
Manufacturer: Distinct By Nature LLC
Category: otc | Type: HUMAN OTC DRUG LABEL
Date: 20201106

ACTIVE INGREDIENTS: ISOPROPYL ALCOHOL 70 mL/100 mL
INACTIVE INGREDIENTS: WATER

70% Rubbing Alcohol